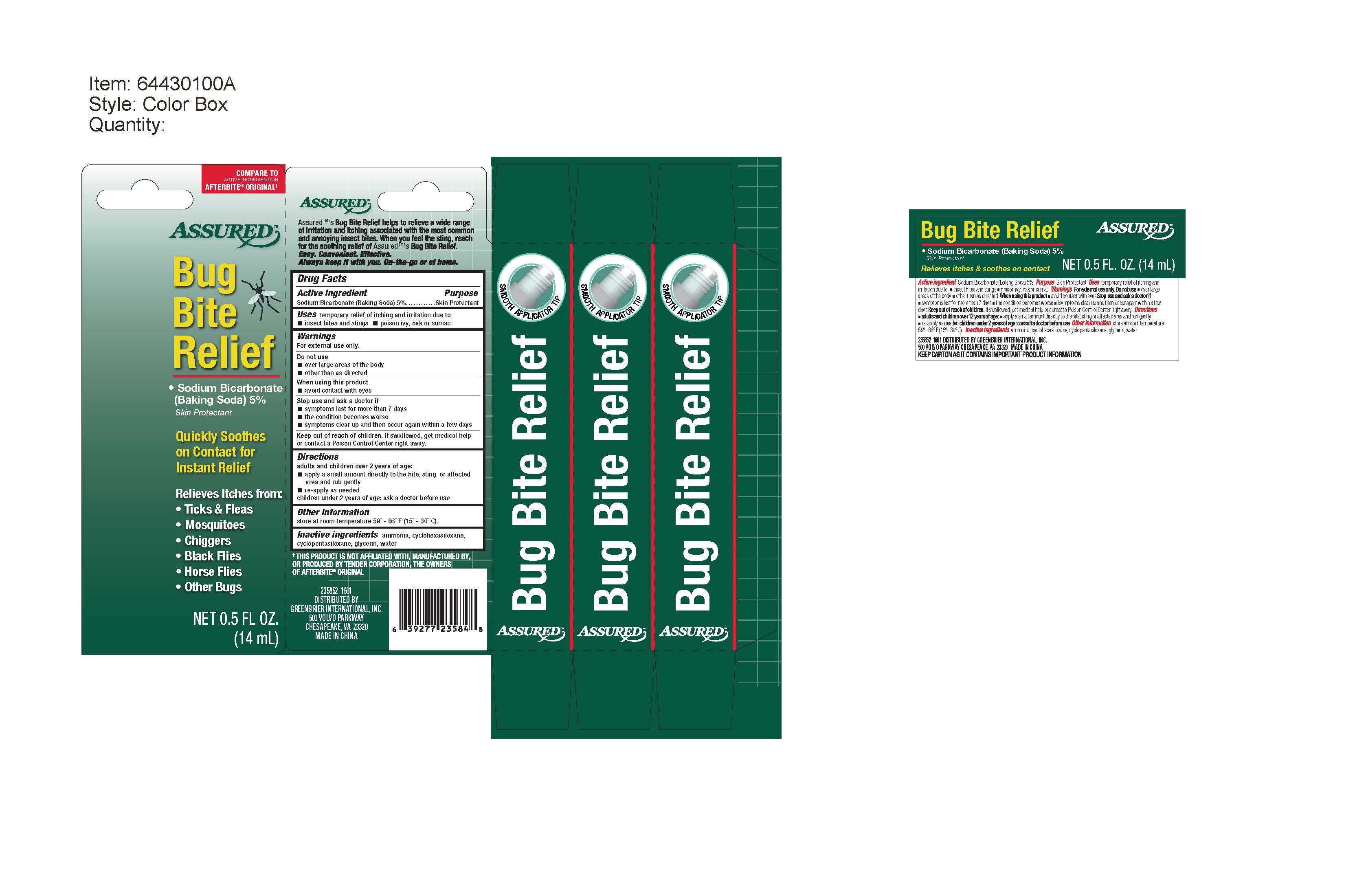 DRUG LABEL: Assured
NDC: 58194-039 | Form: LIQUID
Manufacturer: Shanghai Weierya Daily Chemicals Factory
Category: otc | Type: HUMAN OTC DRUG LABEL
Date: 20160630

ACTIVE INGREDIENTS: SODIUM BICARBONATE 5 g/100 g
INACTIVE INGREDIENTS: AMMONIA; GLYCERIN; CYCLOMETHICONE 6; CYCLOMETHICONE 5; WATER

Drug Facts

Active ingredient

Sodium Bicarbonate (Baking Soda) 5%

Purpose

Skin Protectant

INDICATIONS AND USAGE

Uses temporary relief of itching and irritation due to

-insect bites and stings -poison ivy, oak or sumac

Warnings

For external use only

Do not use

- over large areas of the body
- other than as directed

When using this product

- avoid contact with eyes

Stop use and ask a doctor if

- symptoms last for more than 7 days
- the condition becomes worse
- symptoms clear up and then occur again within a few days

Keep out of reach of children. If swallowed, get medical help

or contact a Poison Control Center right away.

Directions

adults and children over 2 years of age:

-apply a small amount of directly to the bite, sting or affected

area and rub gently

-re-apply as needed

children under 2 years of age: ask a doctor before use

Other information

store at room temperature 59 - 86 F (15 - 30 C)

Inactive ingredients ammonia, cyclohexasiloxane,

cyclopentasiloxane, glycerin, water

DESCRIPTION

Assured's Bug Bite Relief helps to relieve a wide range

of irritation and itching associated with the most common

and annoying insect bites. When you feel the sting, reach

for the soothing relief of Assured's Bug Bite Relief.

Easy. Convenient. Effective.

Always keep it with you. On - the - go or at home.